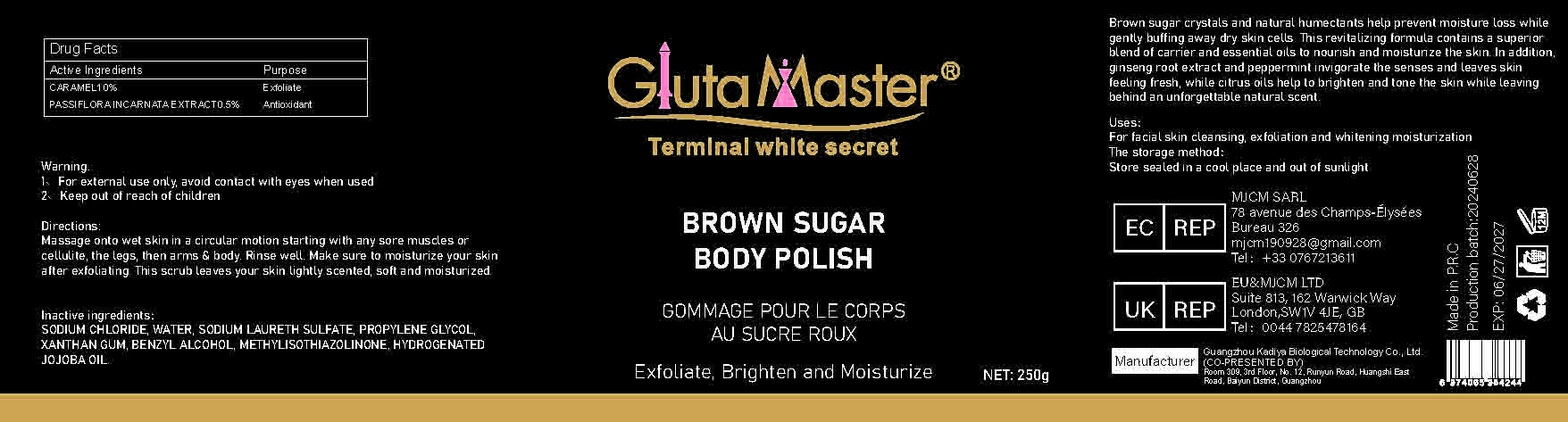 DRUG LABEL: BROWN SUGAR BODY POLISH
NDC: 84423-024 | Form: EMULSION
Manufacturer: Guangzhou Kadiya Biotechnology Co., Ltd.
Category: otc | Type: HUMAN OTC DRUG LABEL
Date: 20240723

ACTIVE INGREDIENTS: CARAMEL 2.5 mg/250 mL; PASSIFLORA INCARNATA TOP 1.25 mg/250 mL
INACTIVE INGREDIENTS: SODIUM CHLORIDE; BENZYL ALCOHOL; HYDROGENATED JOJOBA OIL; WATER; SODIUM LAURETH SULFATE; METHYLISOTHIAZOLINONE; PROPYLENE GLYCOL; XANTHAN GUM

Uses：
For facial skin cleansing, exfoliation and whitening moisturization

INACTIVE INGREDIENT

SODIUM CHLORIDE、WATER、SODIUM LAURETH SULFATE、PROPYLENE GLYCOL、XANTHAN GUM、BENZYL ALCOHOL、METHYLISOTHIAZOLINONE、HYDROGENATED JOJOBA OIL

Warning.
1、For external use only, avoid contact with eyes when used
2、Keep out of reach of children

INDICATIONS AND USAGE

Massage onto wet skin in a circular motion starting with any sore muscles or cellulite, the legs, then arms & body. Rinse well. Make sure to moisturize your skin after exfoliating. This scrub leaves your skin lightly scented, soft and moisturized.

KEEP OUT OF REACH OF CHILDREN SECTION

Active Ingredients
CARAMEL 10%
PASSIFLORA INCARNATA EXTRACT 0.5%

DOSAGE AND ADMINISTRATION

Massage onto wet skin in a circular motion starting with any sore muscles or cellulite, the legs, then arms & body. Rinse well. Make sure to moisturize your skin after exfoliating. This scrub leaves your skin lightly scented, soft and moisturized.

PACKAGE LABEL

Active Ingredients
CARAMEL 10%
PASSIFLORA INCARNATA EXTRACT 0.5%
Uses：
For facial skin cleansing, exfoliation and whitening moisturization
The storage method：
Store sealed in a cool place and out of sunlight
Warning.
1、For external use only, avoid contact with eyes when used
2、Keep out of reach of children
Inactive ingredients：
SODIUM CHLORIDE、WATER、SODIUM LAURETH SULFATE、PROPYLENE GLYCOL、XANTHAN GUM、BENZYL ALCOHOL、METHYLISOTHIAZOLINONE、HYDROGENATED JOJOBA OIL